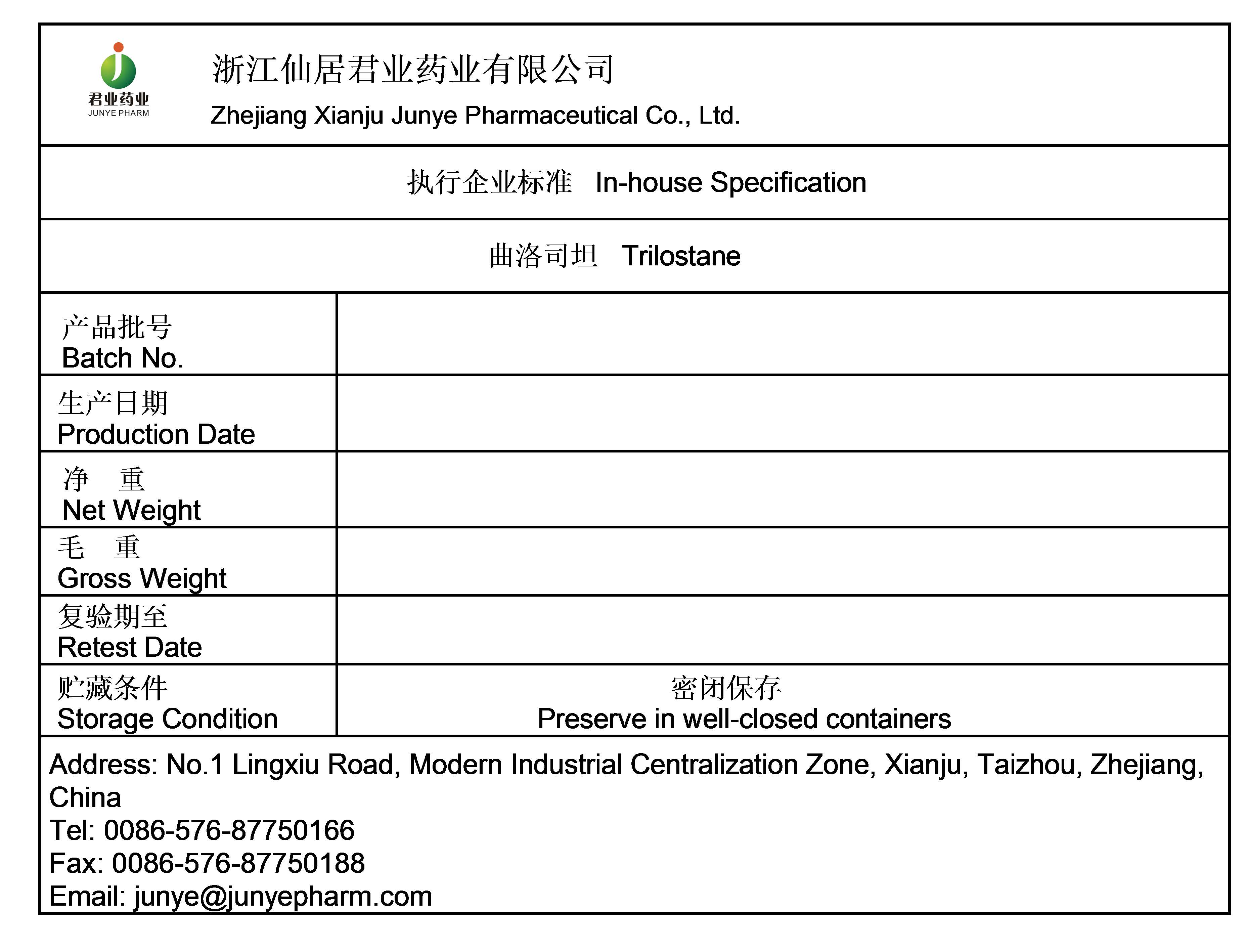 DRUG LABEL: Trilostane
NDC: 69182-004 | Form: POWDER
Manufacturer: Zhejiang Xianju Junye Pharmaceutical Co., Ltd
Category: other | Type: BULK INGREDIENT - ANIMAL DRUG
Date: 20231114

ACTIVE INGREDIENTS: TRILOSTANE 1 kg/1 kg

Trilostane

PACKAGE LABEL

Add image transcription here...